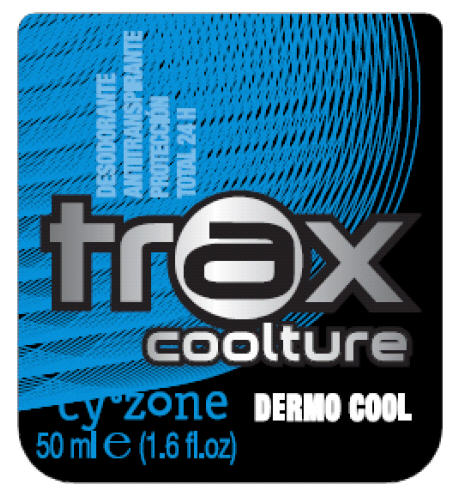 DRUG LABEL: Cyzone 
NDC: 13537-401 | Form: LIQUID
Manufacturer: VENTURA CORPORATION LTDA.
Category: otc | Type: HUMAN OTC DRUG LABEL
Date: 20100809

ACTIVE INGREDIENTS: Aluminum sesquichlorohydrate 10 g/50 mL
INACTIVE INGREDIENTS: Water; steareth-2; steareth-21; cyclomethicone 5; cyclomethicone 6; dicaprylyl carbonate; triclosan; levomenol; benzalkonium chloride; methylparaben; edetate sodium; aloe vera leaf; polyvinyl alcohol; butylated hydroxytoluene; menthol; dipropylene glycol; starch, corn; lemon; west indian lemongrass oil; cinnamon; lavender oil; peppermint oil; olive oil; oregano; rosemary oil; goldenseal; thyme oil; tea tree oil

TRAX Coolture CyZone Dermo Cool Deodorant

Drug Facts

Active Ingredient

Aluminum sesquichlorohydrate 20%

Purpose

Antiperspirant

Uses

- Reduces underarm perspiration
- 24 hour protection

Warnings

For external use only

Do not use on broken skin

Ask a doctor before use if you have Kidney desease

Stop use and ask a doctor if rash or irritation occurs

Keep out of reach of children.If swallowed, get medical help or contact a Poison Control Center right away.

Directions

- Apply to underarms only.

Inactive ingredients

Aqua (water), steareth-2, steareth-21, ppg-15 stearyl ether, cyclopentasiloxane, parfum (fragrance), cyclohexasiloxane, dicaprylyl carbonate, triclosan, bisabolol, benzalkonium chloride, methylparaben, tetrasodium edta, aloe barbadensis leaf juice, polyvinyl alcohol, bht, , menthyl pca, , menthol, dipropylene glycol, saccharomyces/sea salt ferment, zea mays (corn) starch, hydrolyzed corn starch, hydrolyzed corn starch octenylsuccinate, acrylates / c12-22 alkyl methacrylate copolymer, citrus medica limonum peel extract (citrus medica limonum (lemon) peel extract), cymbopogon citratus extract, cinnamomun zeylanicum bark extract, lavandula angustifolia flower extract (lavandula angustifolia (lavender) flower extract), mentha piperita leaf extract(mentha piperita (peppermint) leaf extract), olea europaea leaf extract (olea europaea (olive) leaf extract), origanum vulgare leaf extract, rosmarinus officinalis leaf extract (rosmarinus officinalis (rosemary) leaf extract), hydrastis canadensis root extract (hydrastis canadensis (golden seal) root extract), thymus vulgaris extract (thymus vulgaris (thyme) extract), melaleuca alternifolia leaf (melaleuca alternifolia (tea tree) leaf).

Questions?

Puerto Rico: 1-866-366-3235 (island) 622-3235 (metropolitan area)

PRINCIPAL DISPLAY PANEL - 50 ml Bottle Label

TOTAL 24 H

trax
coolture

Cy°zone
50 ml e (1.6 fl.oz)

DERMO COOL